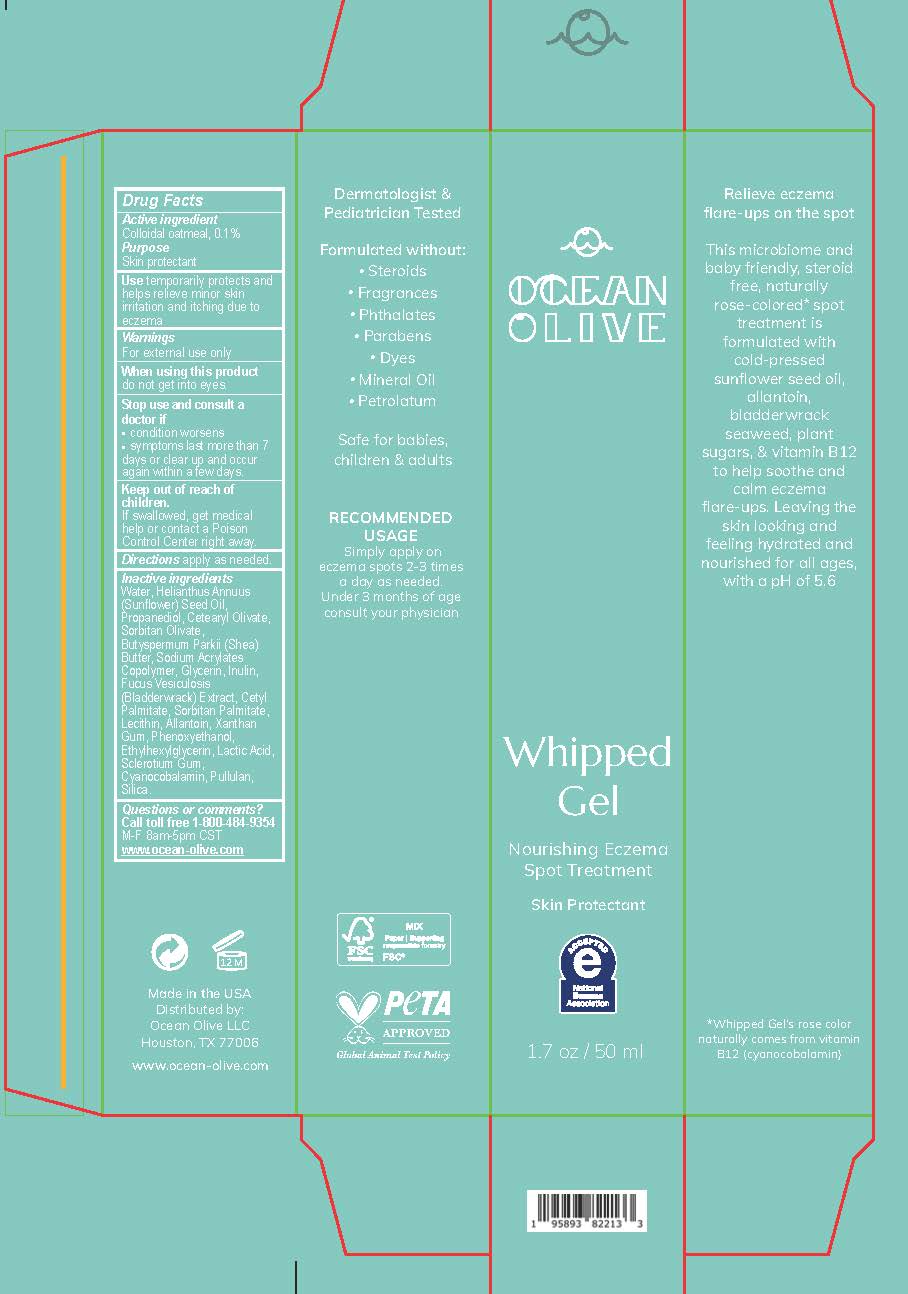 DRUG LABEL: Whipped Gel
NDC: 84293-010 | Form: GEL
Manufacturer: OCEAN OLIVE LLC
Category: otc | Type: HUMAN OTC DRUG LABEL
Date: 20240915

ACTIVE INGREDIENTS: OATMEAL 1 mg/100 g
INACTIVE INGREDIENTS: CETEARYL OLIVATE; SORBITAN OLIVATE; FUCUS VESICULOSUS; SORBITAN MONOPALMITATE; LACTIC ACID; SUNFLOWER OIL; SHEA BUTTER; ACRYLIC ACID/SODIUM ACRYLATE COPOLYMER (1:1; 600 MPA.S AT 0.2%); INULIN; PHENOXYETHANOL; CETYL PALMITATE; LECITHIN, SOYBEAN; XANTHAN GUM; BETASIZOFIRAN; PULLULAN; WATER; PROPANEDIOL; GLYCERIN; SILICON DIOXIDE; ALLANTOIN; ETHYLHEXYLGLYCERIN; CYANOCOBALAMIN

Ocean Olive Whipped Gel

OCEAN OLIVE

Whipped Gel

Nourishing Eczema Spot Treatment

Skin Protectant

Accepted National Eczema Association

1.7 oz / 50 ml

ACTIVE INGREDIENT

Colloidal Oatmeal 0.1%

PURPOSE

Skin Protectant

INDICATIONS AND USAGE

temporarily protects and helps relieve minor skin irritation and itching due to eczema

WARNINGS

For external use only.

When using this product do not get into eyes.

Stop use and consult a doctor if

- conditions worsen
- symptoms last more than 7 days or clear up and occur again within a few days

Keep out of reach of children. If swallowed, get medical help or contact a Poison Control Center right away.

DOSAGE AND ADMINISTRATION

Directions apply as needed.

INACTIVE INGREDIENT

Water, Helianthus Annuus (Sunflower) Seed Oil, Propanediol, Cetearyl Olivate, Sorbitan Olivate, Butyspermum Parkii (Shea) Butter, Sodium Acrylates Copolymer, Glycerin, Inulin, Fucus Vesiculosis (Bladderwrack) Extract, Cetyl Palmitate, Sorbitan Palmitate, Lecithin, Allantoin, Xanthan Gum, Phenoxyethanol, Ethylhexylglycerin, Lactic Acid, Sclerotium Gum, Cyanocobalamin, Pullulan, Silica.

Questions or comments?

Call toll free 1-800-484-9354 M-F 8am-5pm CST

www.ocean-olive.com

RECENT MAJOR CHANGES

Mislabeled section